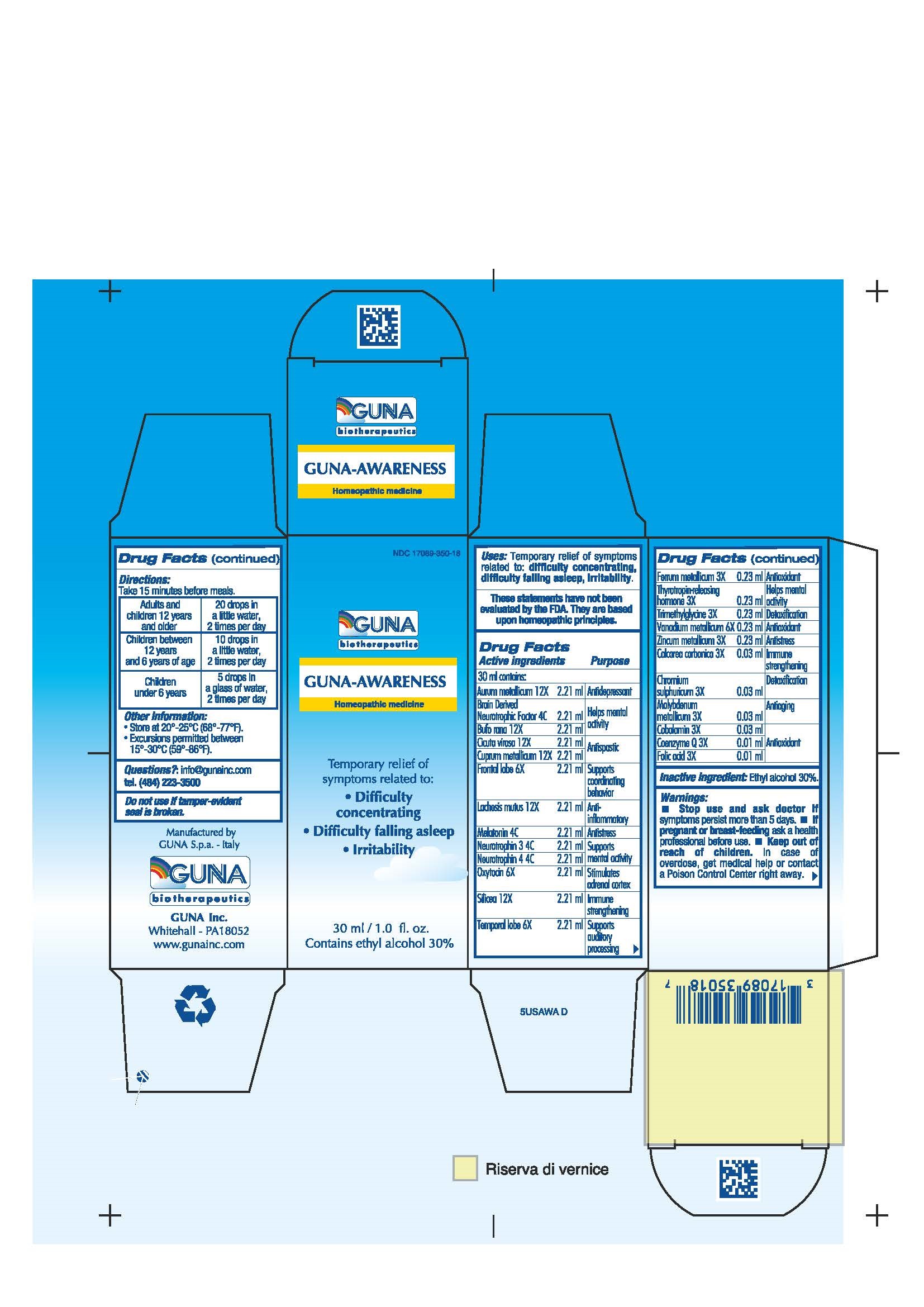 DRUG LABEL: GUNA-AWARENESS
NDC: 17089-350 | Form: SOLUTION/ DROPS
Manufacturer: Guna spa
Category: homeopathic | Type: HUMAN OTC DRUG LABEL
Date: 20221115

ACTIVE INGREDIENTS: GOLD 12 [hp_X]/30 mL; BRAIN-DERIVED NEUROTROPHIC FACTOR HUMAN 4 [hp_C]/30 mL; BUFO BUFO CUTANEOUS GLAND 12 [hp_X]/30 mL; CALCIUM CARBONATE 3 [hp_X]/30 mL; CHROMIC SULFATE 3 [hp_X]/30 mL; CICUTA VIROSA ROOT 12 [hp_X]/30 mL; COBALAMIN 3 [hp_X]/30 mL; UBIDECARENONE 3 [hp_X]/30 mL; COPPER 12 [hp_X]/30 mL; IRON 3 [hp_X]/30 mL; FOLIC ACID 3 [hp_X]/30 mL; SUS SCROFA FRONTAL LOBE 6 [hp_X]/30 mL; LACHESIS MUTA VENOM 12 [hp_X]/30 mL; MELATONIN 4 [hp_C]/30 mL; MOLYBDENUM 3 [hp_X]/30 mL; NEUROTROPHIN-3 4 [hp_C]/30 mL; NEUROTROPHIN-4 4 [hp_C]/30 mL; OXYTOCIN 6 [hp_X]/30 mL; SILICON DIOXIDE 12 [hp_X]/30 mL; SUS SCROFA TEMPORAL LOBE 6 [hp_X]/30 mL; THYROTROPIN ALFA 3 [hp_X]/30 mL; BETAINE 3 [hp_X]/30 mL; VANADIUM 6 [hp_X]/30 mL; ZINC 3 [hp_X]/30 mL
INACTIVE INGREDIENTS: ALCOHOL 9 mL/30 mL

GUNA-AWARENESS

ACTIVE INGREDIENTS/PURPOSE

AURUM METALLICUM 12X ANTIDEPRESSANT
BRAIN DERIVED NEUROTROPHIC FACTOR 4C HELPS MENTAL ACTIVITY
BUFO RANA 12X HELPS MENTAL ACTIVITY
CALCAREA CARBONICA 3X IMMUNE STRENGTHENING
CHROMIUM SULPHURICUM 3X DETOXIFICATION
CICUTA VIROSA 12X ANTISPASTIC
COBALAMIN 3X ANTIOXIDANT
COENZYME Q 3X ANTIOXIDANT
CUPRUM METALLICUM 12X ANTISPASTIC
FERRUM METALLICUM 3X ANTIOXIDANT
FOLIC ACID 3X ANTIOXIDANT
FRONTAL LOBE 6X SUPPORTS COORDINATING BEHAVIOR
LACHESIS MUTUS 12X ANTI-INFLAMMATORY
MELATONIN 4C ANTISTRESS
MOLYBDENUM METALLICUM 3X ANTIAGING
NEUROTROPHIN 3 4C SUPPORTS MENTAL ACTIVITY
NEUROTROPHIN 4 4C SUPPORTS MENTAL ACTIVITY
OXYTOCIN 6X STIMULATES ADRENAL CORTEX
SILICEA 12X IMMUNE STRENGTHENING
TEMPORAL LOBE 6X SUPPORTS AUDITORY PROCESSING
THYROTROPIN-RELEASING HORMONE 3X HELPS MENTAL ACTIVITY
TRIMETHYLGLYCINE 3X DETOXIFICATION
VANADIUM METALLICUM 6X ANTIOXIDANT
ZINCUM METALLICUM 3X ANTISTRESS

USES

Temporary relief of symptoms related to:

- Difficulty concentrating
- Difficulty falling asleep
- Irritability

WARNINGS

- Stop use and ask doctor if symptoms persist more than 5 days or worsen.
- If pregnant or breast-feeding ask a health professional before use.
- Keep out of reach of children. In case of overdose, get medical help or contact a Poison Control Center right away.
- Contains ethyl alcohol 30%

PREGNANCY

If pregnant or breast-feeding ask a doctor before use

WARNINGS

Keep out of reach of children

DIRECTIONS

Take 15 minutes before meals

- Adults and children 12 years and older 20 drops in a little water, 2 times per day
- Children between 12 years and 6 years of age 10 drops in a little water, 2 times per day
- Children under 6 years 5 drops in a glass of water, 2 times per day

QUESTIONS

Questions?: info@gunainc.com, tel. (484) 223-3500

INDICATIONS AND USAGE

- Take 15 minutes before meals

- Inactive ingredient: Ethyl alcohol 30%.